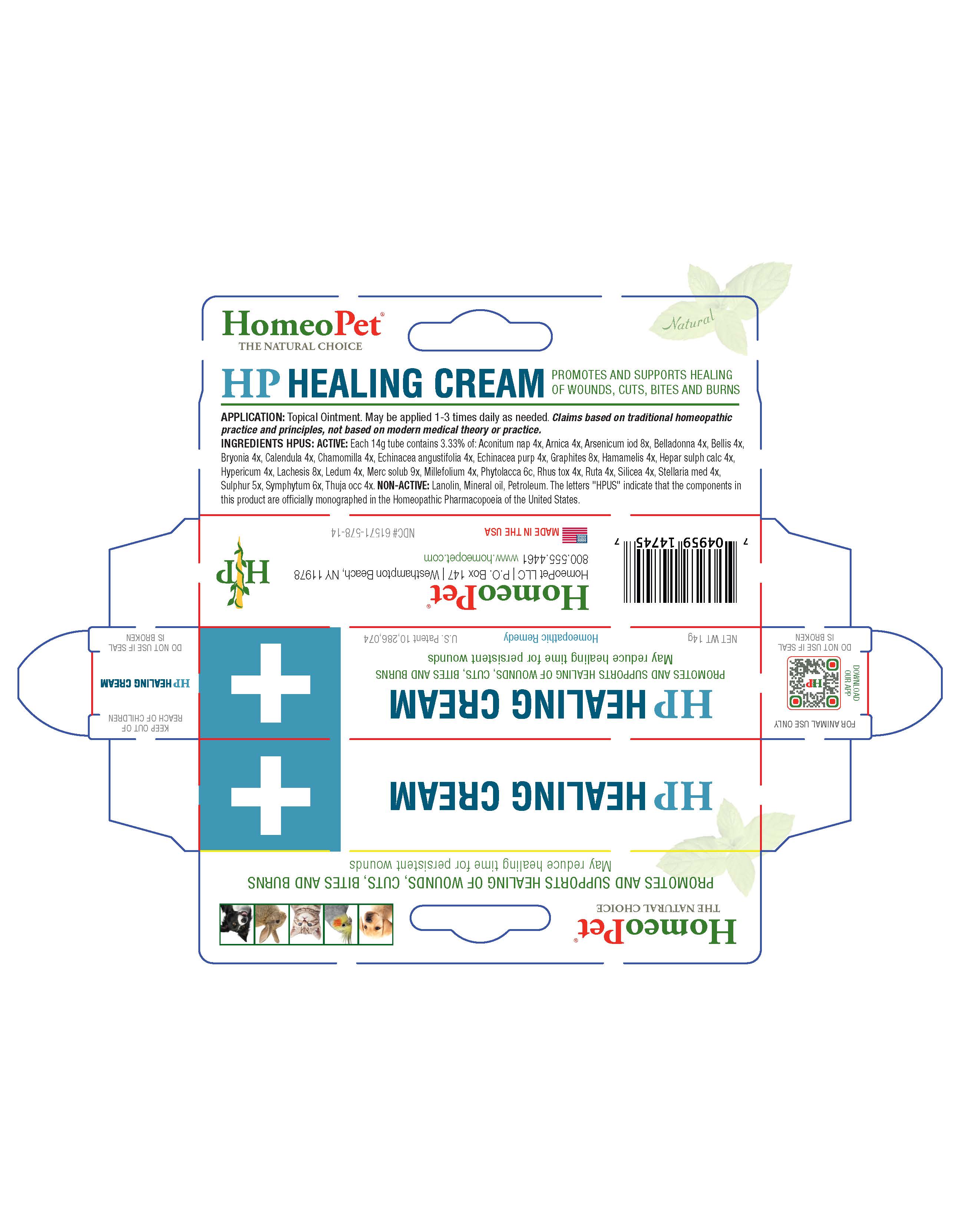 DRUG LABEL: HP Healing 
NDC: 61571-578 | Form: SOLUTION
Manufacturer: HomeoPet, LLC
Category: homeopathic | Type: OTC ANIMAL DRUG LABEL
Date: 20241122

ACTIVE INGREDIENTS: ACONITUM NAPELLUS 4 [hp_X]/14 g; ARNICA MONTANA 4 [hp_X]/14 g; ARSENIC TRIIODIDE 8 [hp_X]/14 g; ATROPA BELLADONNA 4 [hp_X]/14 g; BELLIS PERENNIS 4 [hp_X]/14 g; BRYONIA ALBA ROOT 4 [hp_X]/14 g; CALENDULA OFFICINALIS FLOWERING TOP 4 [hp_X]/14 g; MATRICARIA RECUTITA 4 [hp_X]/14 g; ECHINACEA ANGUSTIFOLIA 4 [hp_X]/14 g; ECHINACEA PURPUREA 4 [hp_X]/14 g; GRAPHITE 8 [hp_X]/14 g; HAMAMELIS VIRGINIANA ROOT BARK/STEM BARK 4 [hp_X]/14 g; CALCIUM SULFIDE 4 [hp_X]/14 g; HYPERICUM PERFORATUM 4 [hp_X]/14 g; LACHESIS MUTA VENOM 8 [hp_X]/14 g; LEDUM PALUSTRE TWIG 4 [hp_X]/14 g; MERCURIUS SOLUBILIS 9 [hp_X]/14 g; ACHILLEA MILLEFOLIUM 4 [hp_X]/14 g; PHYTOLACCA AMERICANA ROOT 6 [hp_C]/14 g; TOXICODENDRON PUBESCENS LEAF 4 [hp_X]/14 g; RUTA GRAVEOLENS FLOWERING TOP 4 [hp_X]/14 g; SILICON DIOXIDE 4 [hp_X]/14 g; STELLARIA MEDIA 4 [hp_X]/14 g; SULFUR  5 [hp_X]/14 g; COMFREY ROOT 6 [hp_X]/14 g; THUJA OCCIDENTALIS LEAFY TWIG 4 [hp_X]/14 g
INACTIVE INGREDIENTS: LANOLIN; PETROLATUM; MINERAL OIL

HP Healing Cream

HP Healing Cream

Promotes and supports healing of wounds, cuts, bites and burns. May reduce healing time for persistent wounds.

Application

Topical ointment. May be applied 1-3 times daily as needed. Claims based on traditional homeopathic practice and principles, not based on modern medical theory or practice.

Ingredients HPUS: Active

Aconitum nap 4x, Arnica 4x, Arsenicum iod 8x, Belladonna 4x, Bellis 4x, Bryonia 4x, Calendula 4x, Chamomilla 4x, Echinacea angustifolia 4x, Echinacea purp 4x, Graphites 8x, Hamamelis 4x, Hepar sulph calc 4x, Hypericum 4x, Lachesis 8x, Ledum 4x, Merc solub 9x, Millefolium 4x, Phytolacca 6c, Rhus tox 4x, Ruta 4x, Silicea 4x, Stellaria med 4x, Sulphur 5x, Symphytum 6x, Thuja occ 4x

Inactive Ingredients

Petroleum, Lanolin, Mineral Oil

PACKAGE LABEL

Add image transcription here...